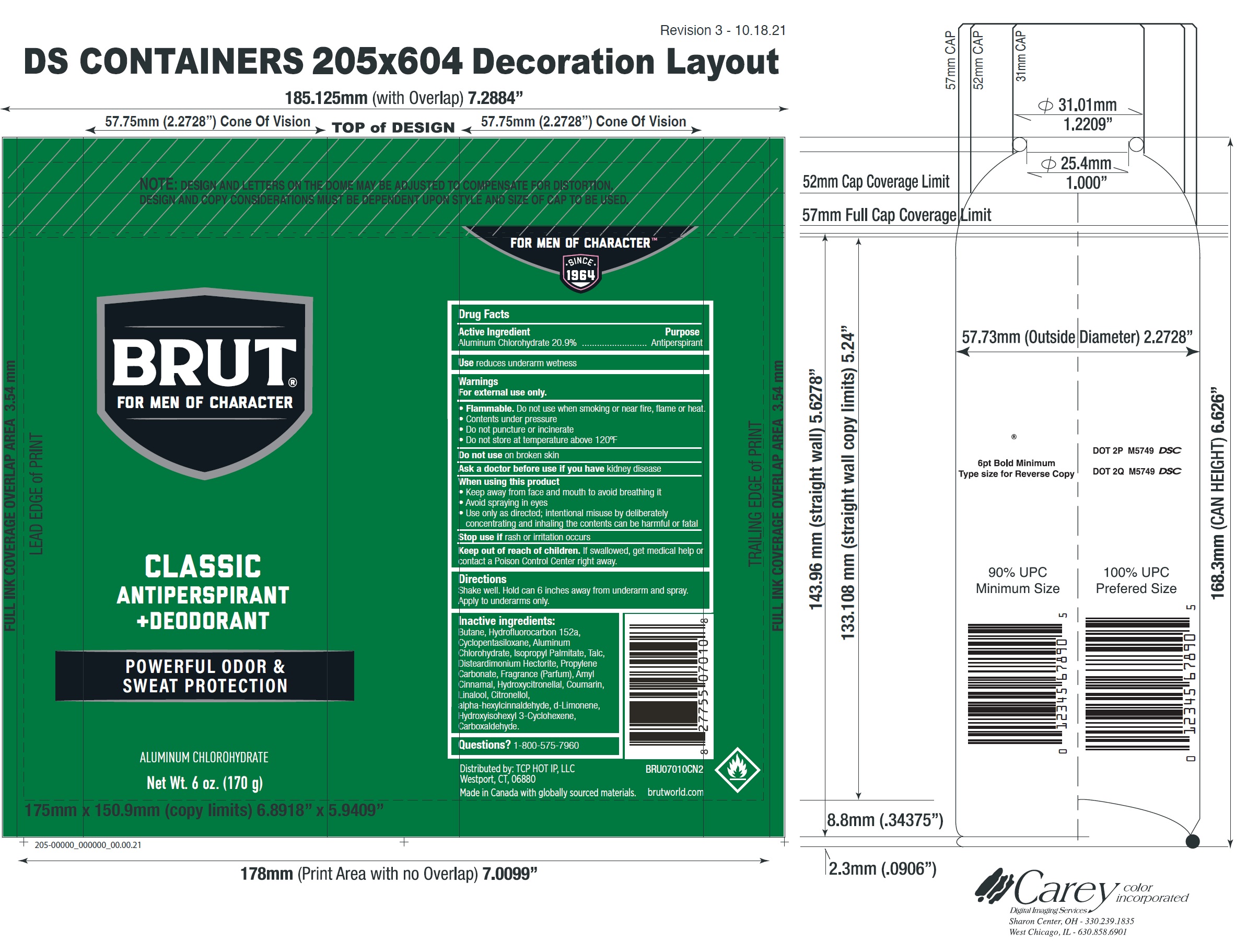 DRUG LABEL: Brut Classic Antiperspirant and Deodorant
NDC: 81277-003 | Form: AEROSOL, SPRAY
Manufacturer: Sodalis USA LLC
Category: otc | Type: HUMAN OTC DRUG LABEL
Date: 20241108

ACTIVE INGREDIENTS: ALUMINUM CHLOROHYDRATE 20.9 g/100 g
INACTIVE INGREDIENTS: BUTANE; 1,1-DIFLUOROETHANE; CYCLOMETHICONE 5; ISOPROPYL PALMITATE; TALC; DISTEARDIMONIUM HECTORITE; PROPYLENE CARBONATE; .ALPHA.-AMYLCINNAMALDEHYDE; HYDROXYCITRONELLAL; COUMARIN; LINALOOL, (+/-)-; .BETA.-CITRONELLOL, (R)-; .ALPHA.-HEXYLCINNAMALDEHYDE; LIMONENE, (+)-; HYDROXYISOHEXYL 3-CYCLOHEXENE CARBOXALDEHYDE

Brut Classic Aerosol Antiperspirant and Deodorant

Active Ingredient

Aluminum Chlorohydrate 20.9%

Purpose

Antiperspirant

Use

reduces underarm wetness

Warnings

For external use only.

- Flammable.Do not use when smoking or near fire, flame or heat.
- Contents under pressure
- Do not puncture or incinerate
- Do not store at temperature above 120ºF

Do not use

on broken skin

Ask a doctor before use if you have

kidney disease

When using this product

- Keep away from face and mouth to avoid breathing it
- Avoid spraying in eyes
- Use only as directed; intentional misuse by deliberately concentrating and inhaling the contents can be harmful or fatal

Stop use if

rash or irritation occurs

Keep out of reach of children.

If swallowed, get medical help or contact a Poison Control Center right away.

Directions

Shake well. Hold can 6 inches away from underarm and spray. Apply to underarms only.

Inactive ingredients:

Butane, Hydrofluorocarbon 152a, Cyclopentasiloxane, Aluminum Chlorohydrate, Isopropyl Palmitate, Talc, Disteardimonium Hectorite, Propylene Carbonate, Fragrance (Parfum), Amyl Cinnamal, Hydroxycitronellal, Coumarin, Linalool, Citronellol, alpha-hexylcinnaldehyde, d-Limonene, Hydroxyisohexyl 3-Cyclohexene, Carboxaldehyde.

Questions?

1-800-575-7960